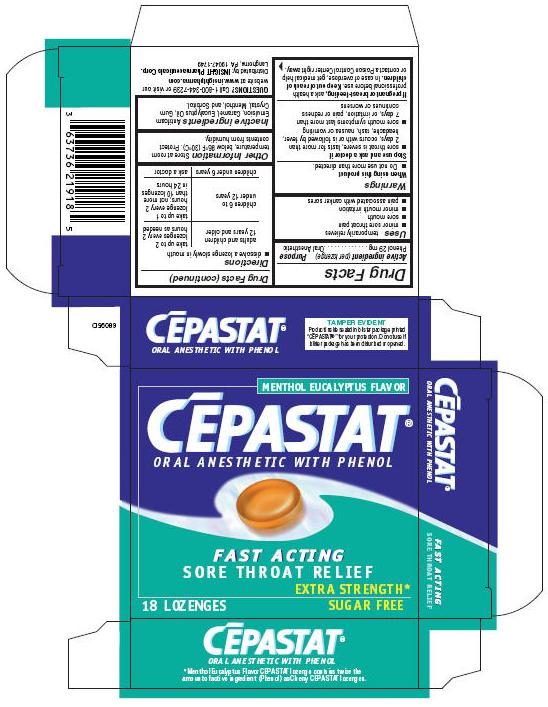 DRUG LABEL: Cepastat
NDC: 63736-219 | Form: LOZENGE
Manufacturer: Insight Pharmaceuticals
Category: otc | Type: HUMAN OTC DRUG LABEL
Date: 20090709

ACTIVE INGREDIENTS: Phenol 29 mg/1 1
INACTIVE INGREDIENTS: Caramel; Eucalyptus Oil; Menthol; Sorbitol

CĒPASTAT®
ORAL ANESTHETIC WITH PHENOL

Drug Facts

Active ingredient (per lozenge)

Phenol 29 mg

Purpose

Oral Anesthetic

Uses

temporarily relieves

- minor sore throat pain
- sore mouth
- minor mouth irritation
- pain associated with canker sores

Warnings

When using this product

- Do not use more than directed.

Stop use and ask a doctor if

- sore throat is severe, lasts for more than 2 days, occurs with or is followed by fever, headache, rash, nausea or vomiting
- sore mouth symptoms last more than 7 days, or irritation, pain or redness continues or worsens

PREGNANCY OR BREAST FEEDING

If pregnant or breast-feeding, ask a health professional before use.

Keep out of reach of children. In case of overdose, get medical help or contact a Poison Control Center right away.

Directions

- dissolve a lozenge slowly in mouth

adults and children 12 years and older | take up to 2 lozenges every 2 hours as needed
children 6 to under 12 years | take up to 1 lozenge every 2 hours; not more than 10 lozenges in 24 hours
children under 6 years | ask a doctor

Other Information

Store at room temperature, below 86°F (30°C). Protect contents from humidity.

Inactive ingredients

Antifoam Emulsion, Caramel, Eucalyptus Oil, Gum Crystal, Menthol, and Sorbitol.

QUESTIONS?

Call 1-800-344-7239 or visit our website at www.insightpharma.com

Distributed by: INSIGHT Pharmaceuticals Corp.
Langhorne, PA 19047-1749

PRINCIPAL DISPLAY PANEL - 18 Lozenges carton

MENTHOL EUCALYPTUS FLAVOR

CĒPASTAT®
ORAL ANESTHETIC WITH PHENOL

FAST ACTING
SORE THROAT RELIEF
EXTRA STRENGTH*

18 LOZENGES
SUGAR FREE